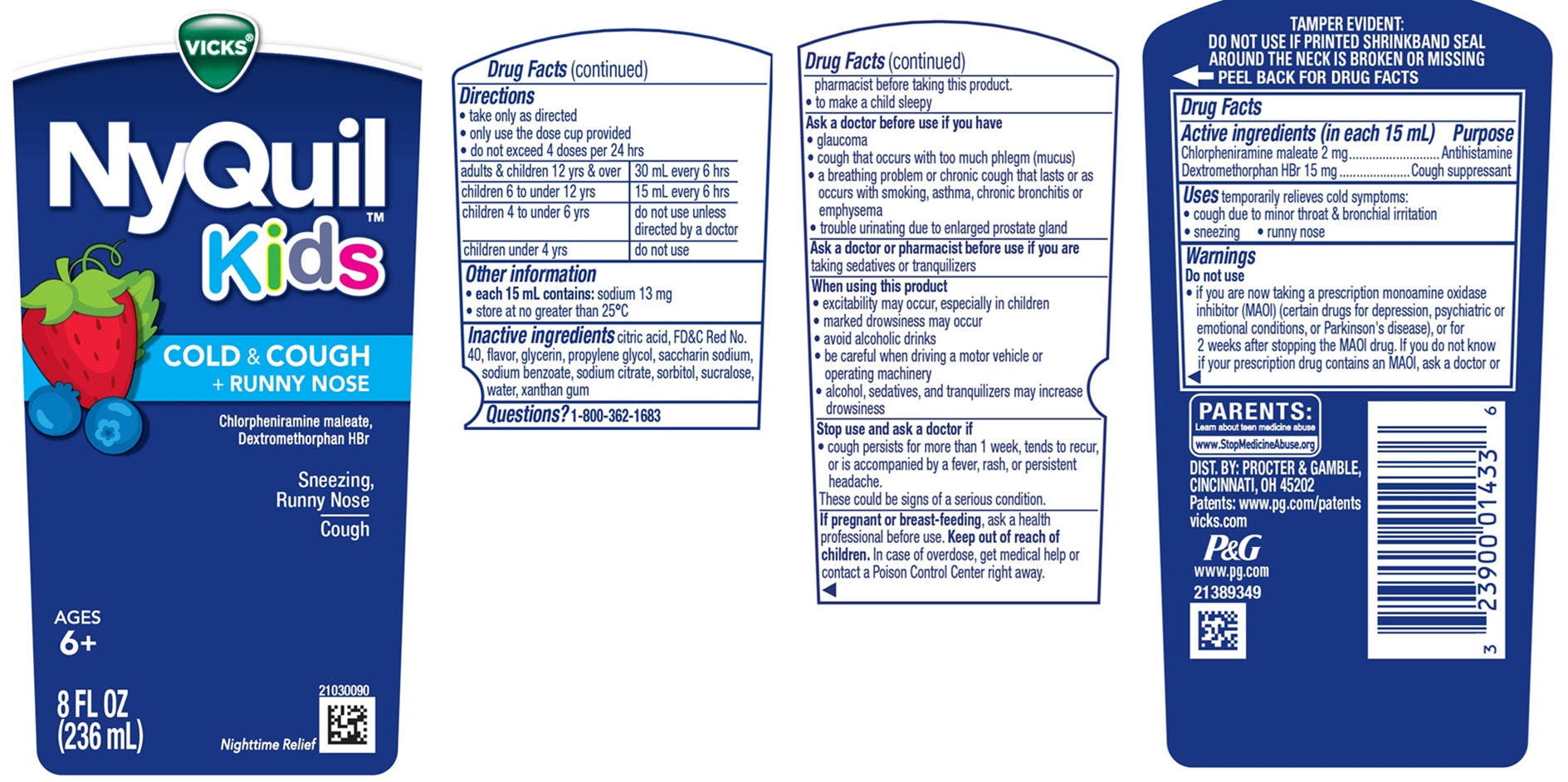 DRUG LABEL: Vicks NyQuil Kids BERRY
NDC: 69423-779 | Form: LIQUID
Manufacturer: The Procter & Gamble Manufacturing Company
Category: otc | Type: HUMAN OTC DRUG LABEL
Date: 20251202

ACTIVE INGREDIENTS: CHLORPHENIRAMINE MALEATE 2 mg/15 mL; DEXTROMETHORPHAN HYDROBROMIDE 15 mg/15 mL
INACTIVE INGREDIENTS: ANHYDROUS CITRIC ACID; FD&C RED NO. 40; PROPYLENE GLYCOL; WATER; SODIUM CITRATE; SUCRALOSE; SACCHARIN SODIUM; SODIUM BENZOATE; GLYCERIN; SORBITOL; XANTHAN GUM

VICKS®NyQuil™ Kids BERRY
COLD & COUGH + RUNNY NOSE

Drug Facts

Active ingredients (in each 15 mL)

Chlorpheniramine maleate 2 mg
Dextromethorphan HBr 15 mg

Purpose

Antihistamine
Cough suppressant

Uses

temporarily relieves cold symptoms:

- cough due to minor throat & bronchial irritation
- sneezing
- runny nose

Warnings

Do not use
• If you are now taking a prescription monoamine oxidase inhibitor (MAOI) (certain drugs for depression, psychiatric or emotional conditions, or Parkinson's disease), or for 2 weeks after stopping the MAOI drug. If you do not know if your prescription drug contains an MAOI, ask a doctor or pharmacist before taking this product.

• to make a child sleepy

Ask a doctor before use if you have

- glaucoma
- cough that occurs with too much phlegm (mucus)
- a breathing problem or chronic cough that lasts or as occurs with smoking, asthma, chronic bronchitis or emphysema
- trouble urinating due to enlarged prostate gland

Ask a doctor or pharmacist before use if you are

taking sedatives or tranquilizers.

When using this product

- excitability may occur, especially in children
- marked drowsiness may occur
- avoid alcoholic drinks
- be careful when driving a motor vehicle or operating machinery
- alcohol, sedatives, & tranquilizers may increase drowsiness

Stop use and ask a doctor if

- cough lasts more than 1 week, tends to recur, or is accompanied by fever, rash, or persistent headache.
  These could be signs of a serious condition.

If pregnant or breast-feeding,

ask a health professional before use.

OVERDOSAGE

In case of overdose, get medical help or contact a Poison Control Center right away.

Directions

- take only as directed
- only use the dose cup provided
- do not exceed 4 doses per 24 hrs

adults & children 12 yrs & over | 30 mL every 6 hrs
children 6 to under 12 yrs | 15 mL every 6 hrs
children 4 to under 6 yrs | do not use unless directed by a doctor
children under 4 yrs | do not use

Other information

- each 15 mL contains: sodium 13 mg
- Store at no greater than 25°C

Inactive ingredients

citric acid, FD&C Red No. 40, flavor, glycerin, propylene glycol, saccharin sodium, sodium benzoate, sodium citrate, sorbitol, sucralose, water, xanthan gum

Questions?

1-800-362-1683

TAMPER EVIDENT: DO NOT USE IF PRINTED SHRINKBAND ON BOTTLE IS BROKEN OR MISSING.

DIST. BY PROCTER & GAMBLE,
CINCINNATI OH 45202

PRINCIPAL DISPLAY PANEL - 236 ml Bottle Label

VICKS®NyQuil™

Kids

BERRY

COLD & COUGH + RUNNY NOSE

Chlorpheniramine maleate,

Dextromethorphan HBr

Sneezing, Runny Nose

Cough

AGES 6+

Nighttime Relief

FREE OF ALCOHOL

& ACETAMINOPHEN

8 FL OZ (236 mL)